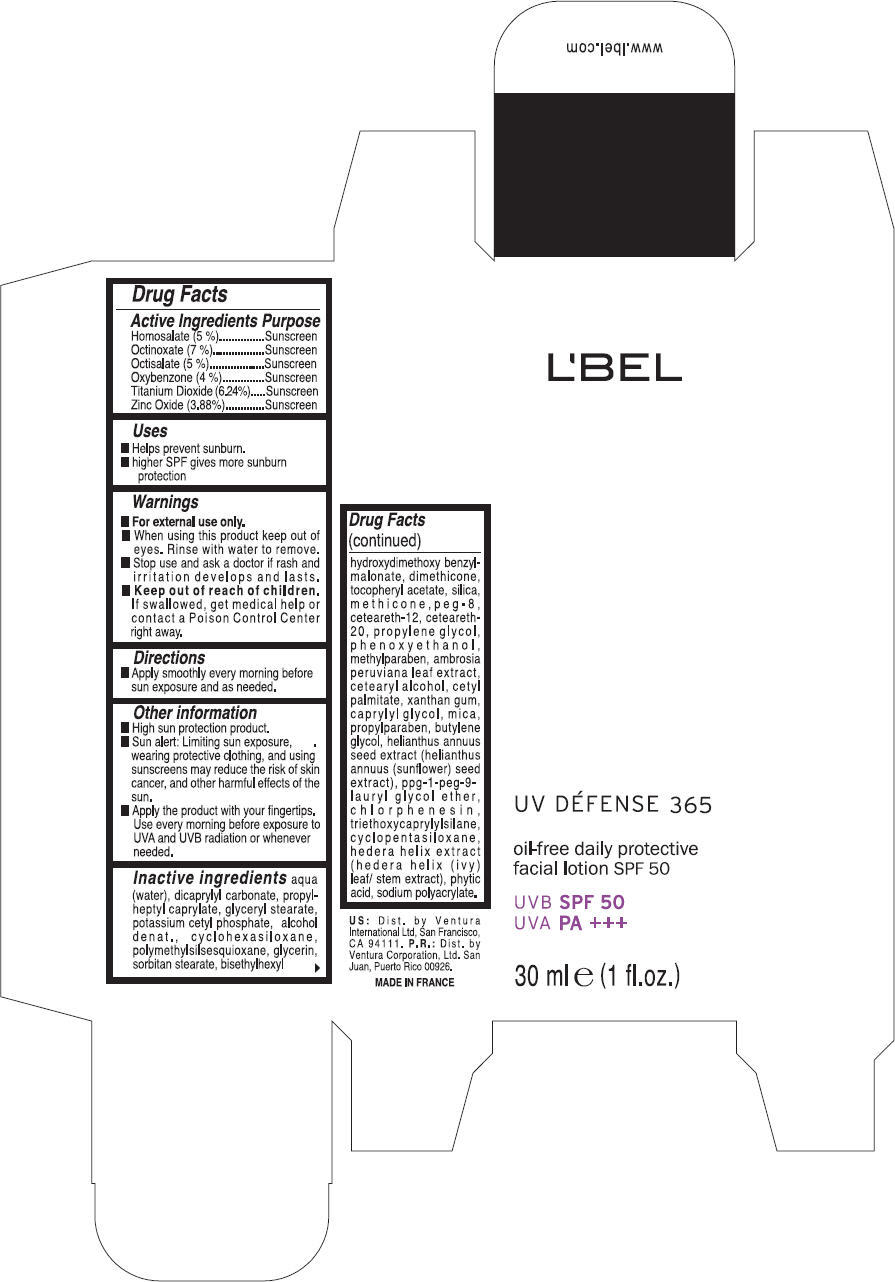 DRUG LABEL: LBEL UV DEFENSE 365
NDC: 14783-094 | Form: LOTION/SHAMPOO
Manufacturer: Ventura International  Ltd. (San Juan, P.R)
Category: otc | Type: HUMAN OTC DRUG LABEL
Date: 20110826

ACTIVE INGREDIENTS: Homosalate 0.05 g/1 mL; Octinoxate 0.07 g/1 mL; Octisalate 0.05 g/1 mL; Oxybenzone 0.04 g/1 mL; Titanium Dioxide 0.0624 g/1 mL; Zinc Oxide 0.0388 g/1 mL
INACTIVE INGREDIENTS: water; dicaprylyl carbonate; propylheptyl caprylate; glyceryl monostearate; potassium cetyl phosphate; cyclomethicone 6; glycerin; sorbitan monostearate; dimethicone; polyoxyl 20 cetostearyl ether; silicon dioxide; cetostearyl alcohol; ceteareth-12; cetyl palmitate; polyethylene glycol 400; propylene glycol; phenoxyethanol; methylparaben; ambrosia peruviana leaf; xanthan gum; caprylyl glycol; mica; propylparaben; triethoxycaprylylsilane; butylene glycol; sunflower seed; chlorphenesin; cyclomethicone 5; hedera helix top; phytic acid

L'BEL
UV DÉFENSE 365

Drug Facts

ACTIVE INGREDIENT

Active Ingredients | Purpose
Homosalate (5 %) | Sunscreen
Octinoxate (7 %) | Sunscreen
Octisalate (5 %) | Sunscreen
Oxybenzone (4 %) | Sunscreen
Titanium Dioxide (6.24%) | Sunscreen
Zinc Oxide (3.88%) | Sunscreen

Uses

- Helps prevent sunburn.
- higher SPF gives more sunburn protection

Warnings

- For external use only.

- When using this product keep out of eyes. Rinse with water to remove.

- Stop use and ask a doctor if rash and irritation develops and lasts.

- Keep out of reach of children. If swallowed, get medical help or contact a Poison Control Center right away.

Directions

- Apply smoothly every morning before sun exposure and as needed.

Other information

- High sun protection product.
- Sun alert: Limiting sun exposure, wearing protective clothing, and using sunscreens may reduce the risk of skin cancer, and other harmful effects of the sun.
- Apply the product with your fingertips. Use every morning before exposure to UVA and UVB radiation or whenever needed.

Inactive ingredients

aqua (water), dicaprylyl carbonate, propylheptyl caprylate, glyceryl stearate, potassium cetyl phosphate, alcohol denat., cyclohexasiloxane, polymethylsilsesquioxane, glycerin, sorbitan stearate, bisethylhexyl hydroxydimethoxy benzylmalonate, dimethicone, tocopheryl acetate, silica, methicone, peg-8, ceteareth-12, ceteareth-20, propylene glycol, phenoxyethanol, methylparaben, ambrosia peruviana leaf extract, cetearyl alcohol, cetyl palmitate, xanthan gum, caprylyl glycol, mica, propylparaben, butylene glycol, helianthus annuus seed extract (helianthus annuus (sunflower) seed extract), ppg-1-peg-9-lauryl glycol ether, chlorphenesin, triethoxycaprylylsilane, cyclopentasiloxane, hedera helix extract (hedera helix (ivy) leaf/ stem extract), phytic acid, sodium polyacrylate.

Dist. by Ventura International Ltd, San Francisco, CA 94111.

PRINCIPAL DISPLAY PANEL - 30 ml Carton

L'BEL

UV DÉFENSE 365

oil-free daily protective
facial lotion SPF 50

UVB SPF 50
UVA PA +++

30 ml e (1 fl. oz.)